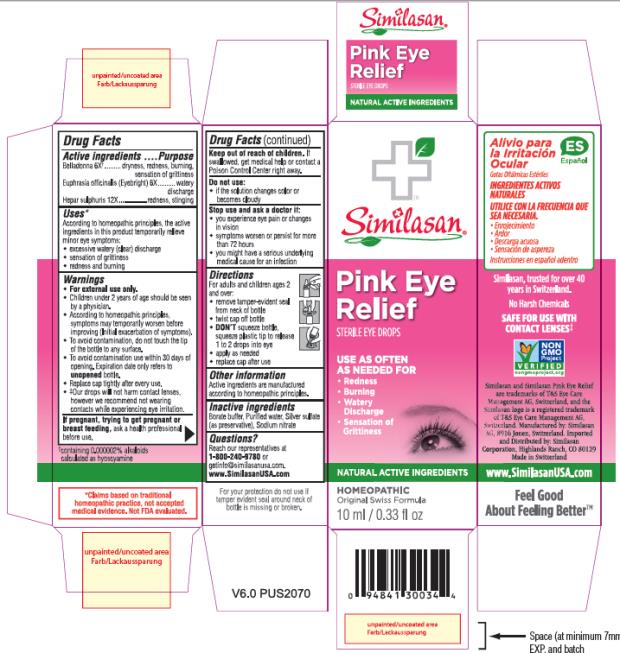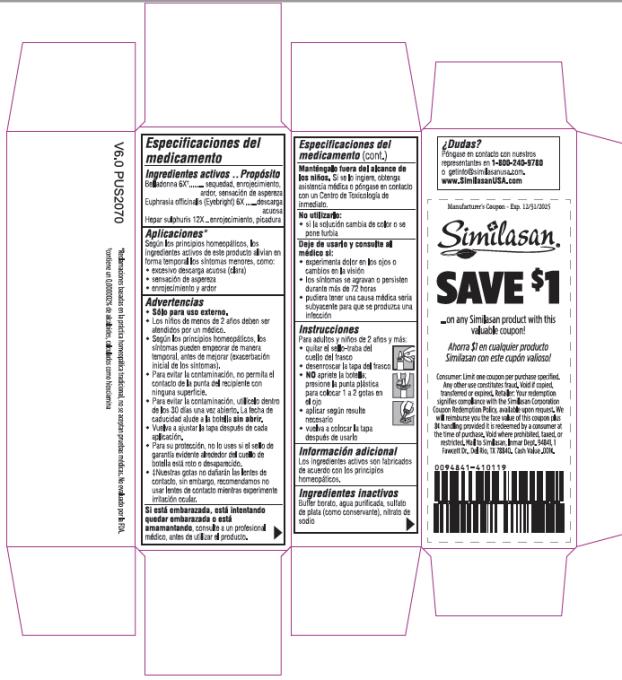 DRUG LABEL: Pink Eye Relief
NDC: 53799-365 | Form: SOLUTION/ DROPS
Manufacturer: Similasan AG
Category: homeopathic | Type: HUMAN OTC DRUG LABEL
Date: 20211007

ACTIVE INGREDIENTS: ATROPA BELLADONNA 6 [hp_X]/10 mL; EUPHRASIA STRICTA 6 [hp_X]/10 mL; CALCIUM SULFIDE 12 [hp_X]/10 mL
INACTIVE INGREDIENTS: WATER; SILVER SULFATE; SODIUM NITRATE; SODIUM BORATE

Pink Eye Relief

Drug Facts

Active ingredients

Belladonna 6X†

†containing 0.000002% alkaloids calculated as hyoscyamine

Purpose

dryness, redness, burning, sensation of grittiness

Active ingredients

Euphrasia officinalis (Eyebright) 6X

Purpose

watery discharge

Active ingredients

Hepar sulphuris 12X

Purpose

redness, stinging

Uses*

According to homeopathic principles, the active ingredients in this product temporarily relieve minor eye symptoms:

• excessive watery (clear) discharge

• sensation of grittiness

• redness and burning

Warnings

• For external use only.

• Children under 2 years of age should be seen by a physician.

• According to homeopathic principles, symptoms may temporarily worsen before improving (Initial exacerbation of symptoms).

• To avoid contamination, do not touch the tip of the bottle to any surface.

• To avoid contamination use within 30 days of opening. Expiration date only refers to unopened bottle.

• Replace cap tightly after every use.

• ‡Our drops will not harm contact lenses, however we recommend not wearing contacts while experiencing eye irritation.

Keep out of reach of children.

If swallowed, get medical help or contact a Poison Control Center right away.

Do not use:

• if the solution changes color or becomes cloudy

Stop use and ask a doctor if:

• you experience eye pain or changes in vision

• symptoms worsen or persist for more than 72 hours

• you might have a serious underlying medical cause for an infection

Directions

For adults and children ages 2 and over:

• remove tamper-evident seal from neck of bottle

• twist cap off bottle

• DON’T squeeze bottle, squeeze plastic tip to release 1 to 2 drops into eye

• apply as needed

• replace cap after use

Other information

Active ingredients are manufactured according to homeopathic principles.

Inactive ingredients

Borate buffer, Purified water, Silver sulfate (as preservative), Sodium nitrate

Questions?

Reach our representatives at 1-800-240-9780 or getinfo@similasanusa.com.
www.SimilasanUSA.com

For your protection do not use if tamper evident seal around neck of bottle is missing or broken.

*Claims based on traditional homeopathic practice, not accepted medical evidence. Not FDA evaluated.

PRINCIPAL DISPLAY PANEL

Similasan
Pink eye
Relief
10 mL/ 0.33 fl oz